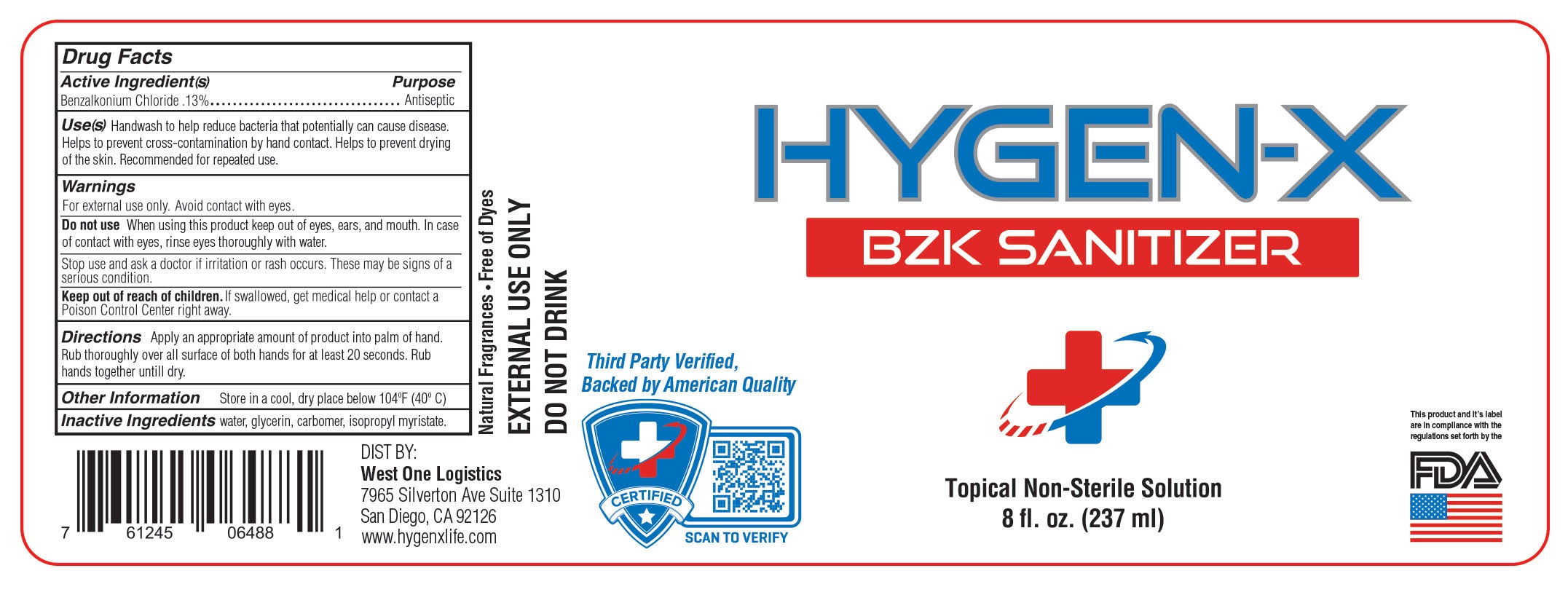 DRUG LABEL: Hand Sanitizer
NDC: 77856-6866 | Form: LIQUID
Manufacturer: West One Logistics, LLC.
Category: otc | Type: HUMAN OTC DRUG LABEL
Date: 20200909

ACTIVE INGREDIENTS: BENZALKONIUM CHLORIDE 5 mg/3785 mg
INACTIVE INGREDIENTS: BENZYL ALCOHOL 1.9 mg/3785 mg; FRAGRANCE LAVENDER & CHIA F-153480 3.8 mg/3785 mg; WATER 3774 mg/3785 mg

BZK Hygen-x

Active Ingredient(s)

Alcohol 80% v/v. Purpose: Antiseptic

Purpose

Antiseptic, Hand Sanitizer

Use

Hand Sanitizer to help reduce bacteria that potentially can cause disease. For use when soap and water are not available.

Warnings

For external use only.

Do not use

- in children less than 2 months of age
- on open skin wounds

When using this product keep out of eyes, ears, and mouth. In case of contact with eyes, rinse eyes thoroughly with water.
Stop use and ask a doctor if irritation or rash occurs. These may be signs of a serious condition.
Keep out of reach of children. If swallowed, get medical help or contact a Poison Control Center right away.

Stop use and ask a doctor if irritation or rash occurs. These may be signs of a serious condition.

Keep out of reach of children. If swallowed, get medical help or contact a Poison Control Center right away.

Directions

- Place enough product on hands to cover all surfaces. Rub hands together until dry.
- Supervise children under 6 years of age when using this product to avoid swallowing.

Other information

- Store between 15-30C (59-86F)
- Avoid freezing and excessive heat above 40C (104F)

Inactive ingredients

glycerin, hydrogen peroxide, purified water USP

Safe Handling

Keep out of reach of children.

Package Label - Principal Display Panel

3774 mL NDC: 77856-001-01 JPEG